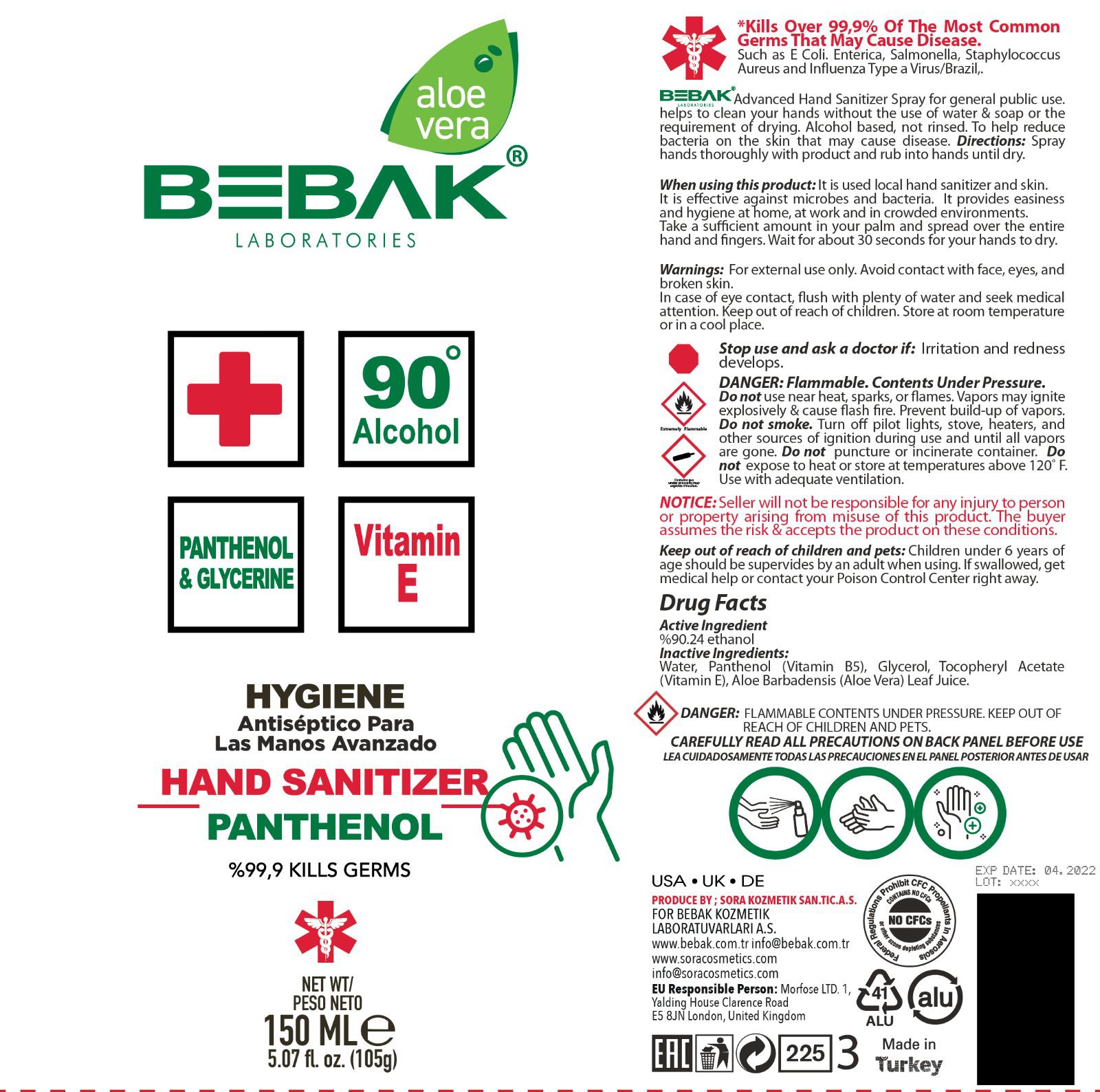 DRUG LABEL: Bebak Hygiene Hand Sanitizer
NDC: 77462-015 | Form: AEROSOL, SPRAY
Manufacturer: SORA KOZMETIK SANAYI TICARET ANONIM SIRKETI
Category: otc | Type: HUMAN OTC DRUG LABEL
Date: 20200911

ACTIVE INGREDIENTS: ALCOHOL 135.26 mL/150 mL
INACTIVE INGREDIENTS: WATER; ALOE VERA LEAF; PANTHENOL; GLYCERIN; .ALPHA.-TOCOPHEROL ACETATE

Bebak Hygiene Hand Sanitizer Spray (aerosol)

Active Ingredient

Ethanol 90.24%

Purpose

Antiseptic

Uses

To help reduce bacteria on skin that may cause disease.

Warnings

For external use only. Avoid contact with face, eyes, and broken skin. In case of eye contact, flush with plenty of water and seek medical attention.

DANGER: Flammable. Contents Under Pressure.

Do not use near heat, sparks or flames. Vapors may ignite explosively and cause flash fire. Prevent build up of vapors.

Do not smoke turn of pilot lights, stove, heaters and other sources of ignition during use and until all vapors are gone.

Do not puncture of incinerate container. Do not expose to heat or store at temperatures above 120F.

Use with adequate ventilation.

Stop use and ask a doctor if: irritation and redness develops.

Keep out of reach of children and pets. Children under 6 years of age should be supervised by an adult when using. If swallowed, get medical help or contact your Poison Control Center right away.

Directions

Spray hands thoroughly with product and rub into hands until dry.

STORAGE AND HANDLING

Store at room temperature or in a cool place.

Inactive Ingredients

Water, Panthenol (Vitamin B5), Glycerol, Tocopheryl Acetate (Vitamin E), Aloe Barbadensis (Aloe Vera) Leaf Juice.